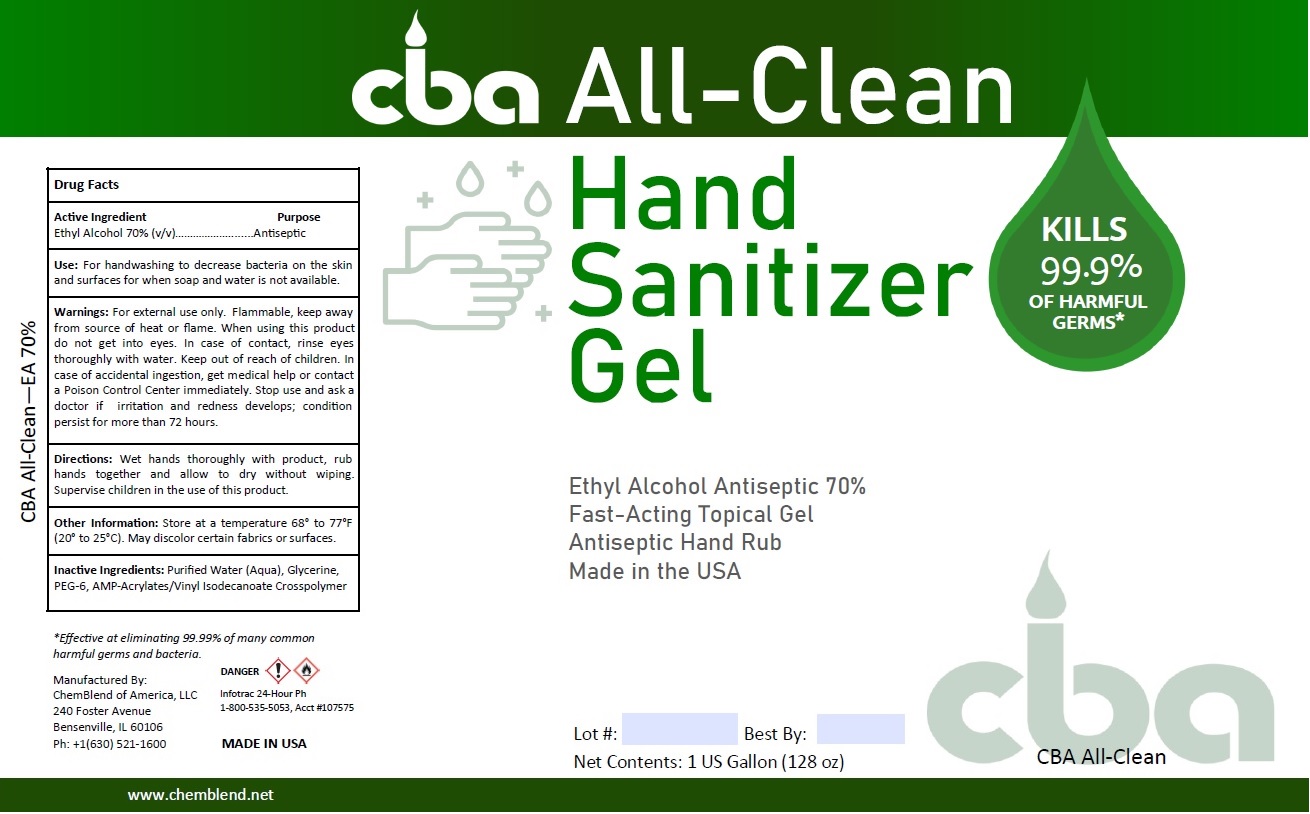 DRUG LABEL: CBA All-Clean Hand Sanitizer Gel
NDC: 74417-300 | Form: GEL
Manufacturer: Chemblend of America, LLC
Category: otc | Type: HUMAN OTC DRUG LABEL
Date: 20200914

ACTIVE INGREDIENTS: ALCOHOL 70 L/100 L
INACTIVE INGREDIENTS: WATER; GLYCERIN; RAPIDGEL EZ1

cba All-Clean Hand Sanitizer Gel

Active Ingredient

Ethyl Alcohol 70% (v/v)

Purpose

Antiseptic

INDICATIONS AND USAGE

Use: For handwashing to decrease bacteria on the skin and surfaces for when soap and water is not available.

WARNINGS

Warnings: For external use only. Flammable, keep away from source of heat or flame. When using this product do not get into eyes. In case of contact, rinse eyes thoroughly with water. Stop use and ask a doctor if irritation and redness develops; condition persist for more than 72 hours.

Keep out of reach of children. In case of accidental ingestion, get medical help or contact a Poison Control Center immediately.

DOSAGE AND ADMINISTRATION

Directions: Wet hands thoroughly with product, rub hands together and allow to dry without wiping. Supervise children in the use of this product.

Other Information: Store at a temperature 68° to 77°F (20° to 25°C). May discolor certain fabrics or surfaces.

INACTIVE INGREDIENT

Inactive Ingredients: Purified Water (Aqua), Glycerine, PEG-6, AMP-Acrylates/Vinyl Isodecanoate Crosspolymer

KILLS 99.9% OF HARMFUL GERMS*

Ethyl Alcohol Antiseptic 70%

Fast-Acting Topical Gel

Antiseptic Hand Rub

Made in the USA

*Effective at eliminating 99.99% of many common harmful germs and bacteria.

Manufactured By:

ChemBlend of America, LLC

240 Foster Avenue

Bensenville, IL 60106

Ph: +1(630) 521-1600

DANGER

Infotrac 24-Hour Ph

1-800-535-5053, Acct #107575

www.chemblend.net

MADE IN USA